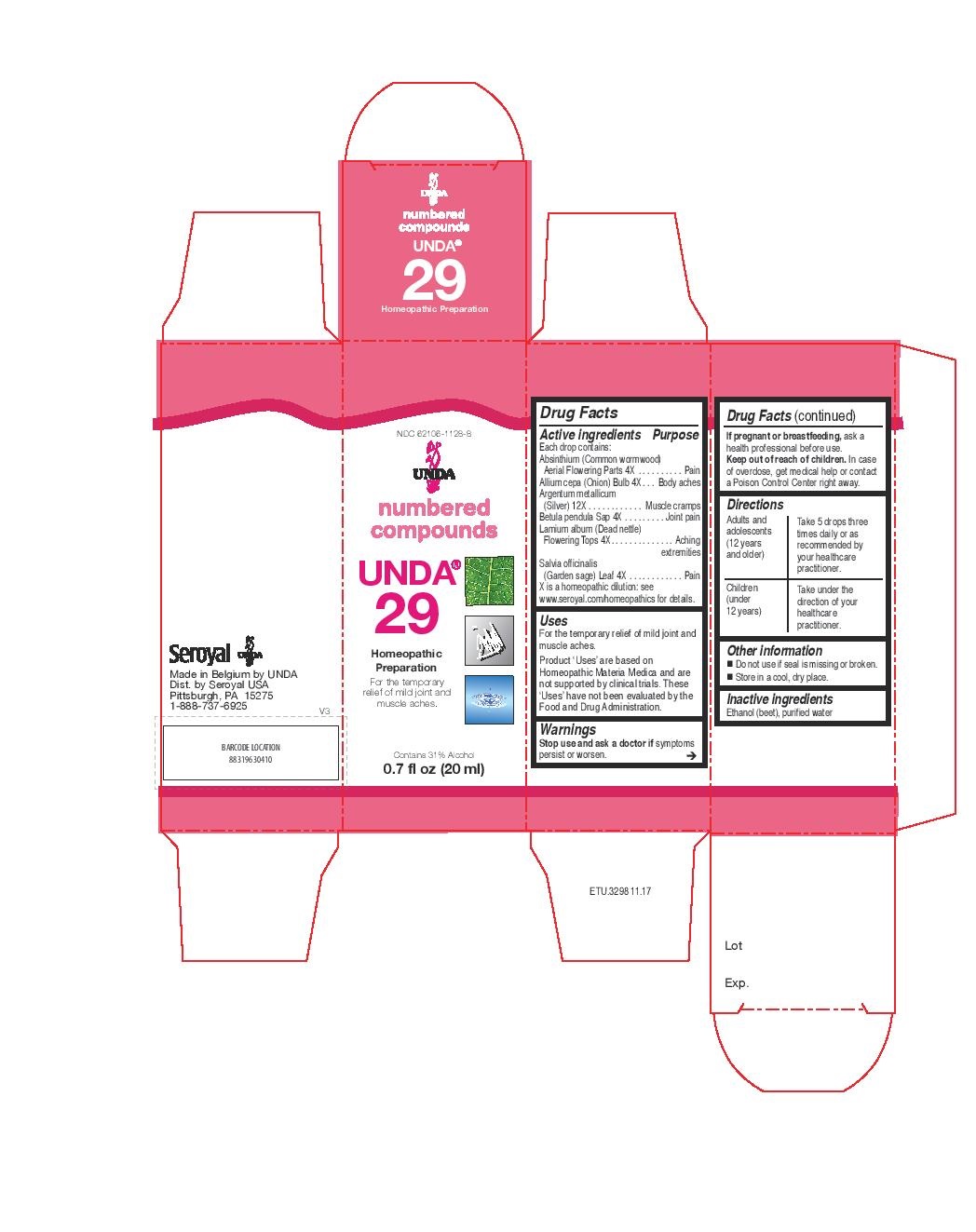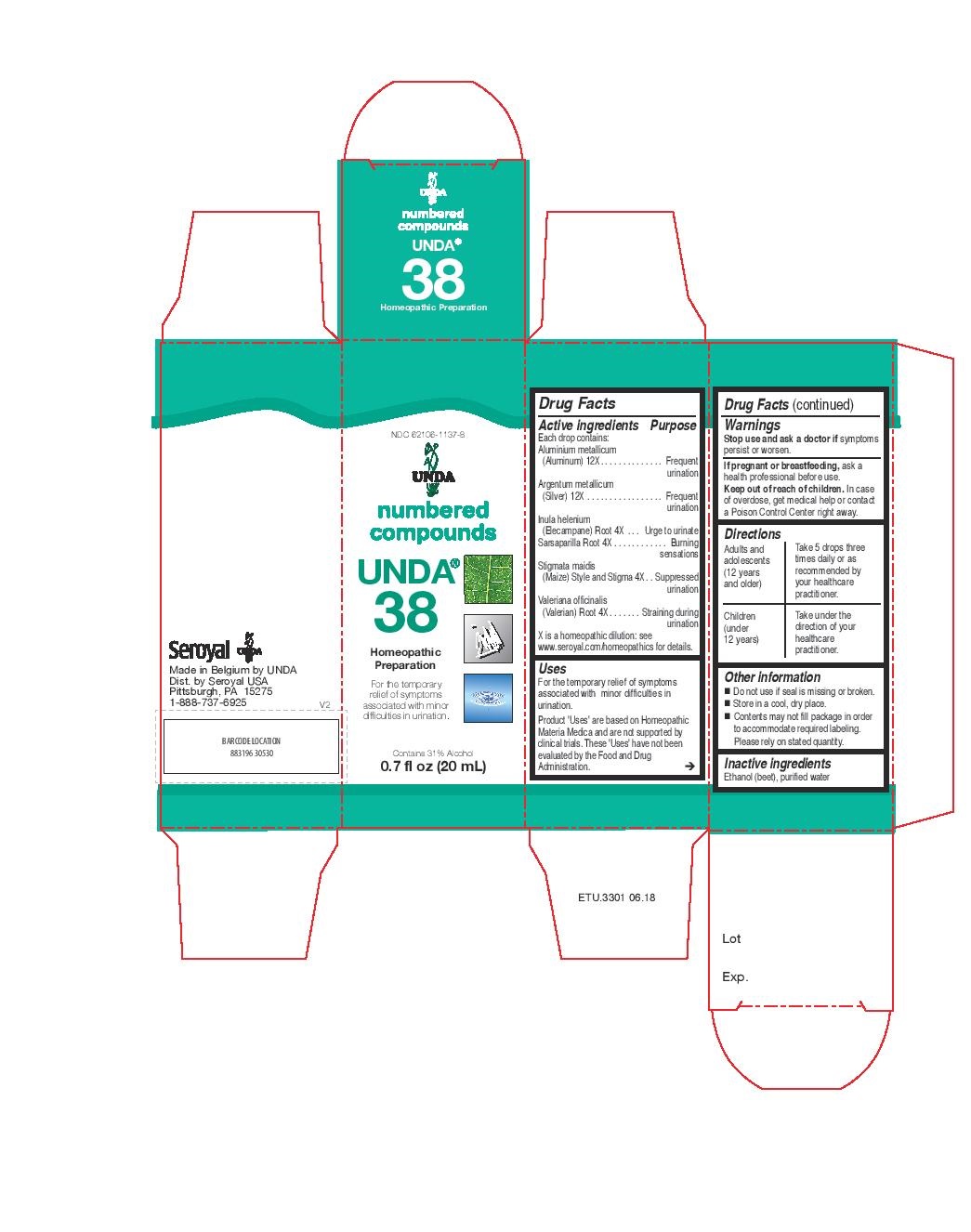 DRUG LABEL: UNDA 29
NDC: 62106-1128 | Form: LIQUID
Manufacturer: Seroyal USA
Category: homeopathic | Type: HUMAN OTC DRUG LABEL
Date: 20221109

ACTIVE INGREDIENTS: LAMIUM ALBUM 4 [hp_X]/20 mL; WORMWOOD 4 [hp_X]/20 mL; ONION 4 [hp_X]/20 mL; SILVER 12 [hp_X]/20 mL; BETULA PENDULA WOOD 4 [hp_X]/20 mL; SAGE 4 [hp_X]/20 mL
INACTIVE INGREDIENTS: ALCOHOL; WATER

UNDA 29 and 38

Active ingredients

Each drop contains:
Absinthium (Common wormwood) Aerial Parts 4X
Allium cepa (Onion) Bulb 4X
Argentum metallicum (Silver) 12X
Betula pendula Sap 4X
Lamium album (Dead nettle) Flowering Tops 4X
Salvia officinalis (Garden sage) Leaf 4X

Uses

For the temporary relief of mild joint and muscle aches.

Warnings
Stop use and ask a doctor if symptoms persist or worsen.

If pregnant or breastfeeding, ask a health professional before use.
Keep out of reach of children.
In case of overdose, get medical help or contact a Poison Control Center right away.

Stop use and ask a doctor if symptoms persist or worsen.

PREGNANCY OR BREAST FEEDING

If pregnant or breastfeeding, ask a health professional before use.

Keep out of reach of children.

OVERDOSAGE

In case of overdose, get medical help or contact a Poison Control Center right away.

Inactive ingredients
Ethanol (beet), purified water

Other information
Do not use if seal is missing or broken.
Store in a cool, dry place.

Directions
Adults and adolescents (12 years and older)

Take 5 drops three times daily or as recommended by your healthcare practitioner.
Children (under 12 years)

Take under the direction of your healthcare practitioner.

Uses

For the temporary relief of mild joint and muscle aches.

Directions
Adults and adolescents (12 years and older)

Take 5 drops three times daily or as recommended by your healthcare practitioner.
Children (under 12 years)

Take under the direction of your healthcare practitioner.

Active ingredients

Each drop contains equal parts of:

Aluminium metallicum (Aluminum) 12X
Argentum metallicum (Silver) 12X
Inula helenium (Elecampane) Root 4X
Sarsaparilla Root 4X
Stigmata maidis (Maize) Style and Stigma 4X
Valeriana officinalis (Valerian) Root 4X

Uses
For the relief of symptoms associated with
minor difficulties in urination.

Warnings

Stop use and ask a doctor if symptoms persist or worsen.
If pregnant or breastfeeding, ask a health professional before use.
Keep out of reach of children.
In case of overdose, get medical help or contact a Poison Control Center right away.

Stop use and ask a doctor if symptoms persist or worsen.

PREGNANCY OR BREAST FEEDING

If pregnant or breastfeeding, ask a health professional before use.

Keep out of reach of children.

OVERDOSAGE

In case of overdose, get medical help or contact a Poison Control Center right away.

Inactive ingredients
Ethanol (beet), purified water

Other information
Do not use if seal is missing or broken.
Store in a cool, dry place.

Directions
Adults and adolescents (12 years and older): Take 5 drops three times daily or as
recommended by your healthcare practitioner.
Children (under 12 years): Take under the direction of your
healthcare practitioner.

Uses
For the relief of symptoms associated with
minor difficulties in urination.

Directions
Adults and adolescents (12 years and older): Take 5 drops three times daily or as
recommended by your healthcare practitioner.
Children (under 12 years): Take under the direction of your
healthcare practitioner.

PACKAGE LABEL

NDC 62106-1128-8

UNDA
numbered compounds
UNDA 29
Homeopathic Preparation

For the temporary relief of mild

joint and muscle aches.
Contains 31% Alcohol
0.7 fl oz (20 ml)

PACKAGE LABEL

NDC 62106-1137-8

UNDA
numbered compounds
UNDA 38
Homeopathic Preparation

For the temporary relief of symptoms
associated with minor difficulties in urination.
Contains 31% Alcohol
0.7 fl oz (20 mL)